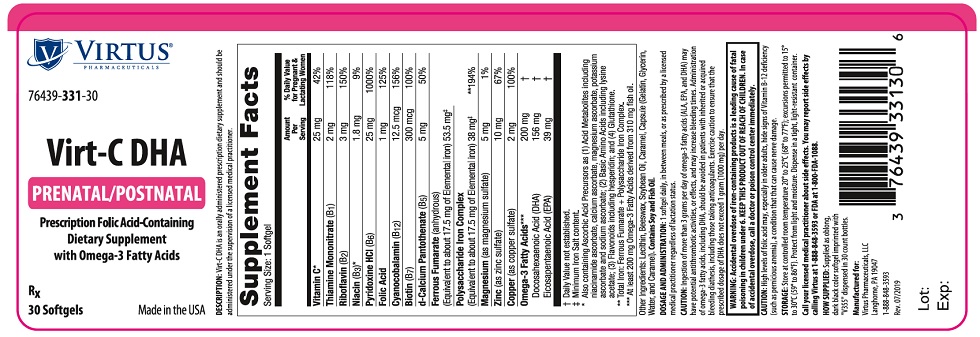 DRUG LABEL: Virt-C DHA
NDC: 76439-331 | Form: CAPSULE, GELATIN COATED
Manufacturer: Virtus Pharmaceuticals
Category: other | Type: DIETARY SUPPLEMENT
Date: 20191108

ACTIVE INGREDIENTS: ASCORBIC ACID 25 mg/1 1; THIAMINE MONONITRATE 2 mg/1 1; RIBOFLAVIN 3 mg/1 1; NIACIN 1.8 mg/1 1; PYRIDOXINE HYDROCHLORIDE 25 mg/1 1; FOLIC ACID 1 mg/1 1; CYANOCOBALAMIN 12.5 ug/1 1; BIOTIN 300 ug/1 1; CALCIUM PANTOTHENATE 5 mg/1 1; FERROUS FUMARATE 53.5 mg/1 1; IRON 38 mg/1 1; MAGNESIUM SULFATE, UNSPECIFIED FORM 5 mg/1 1; ZINC SULFATE, UNSPECIFIED FORM 10 mg/1 1; CUPRIC SULFATE 2 mg/1 1; DOCONEXENT 156 mg/1 1; ICOSAPENT 39 mg/1 1
INACTIVE INGREDIENTS: YELLOW WAX; SOYBEAN OIL; CARAMEL; GELATIN, UNSPECIFIED; GLYCERIN; WATER

Virt-C DHA

DESCRIPTION

Virt-C DHA is an orally administered prescription dietary supplement and should be administered under the supervision of a licensed medical practitioner.

Supplement Facts
Serving Size: 1 Softgel
 | Amount Per Serving | % Daily Value for Pregnant & Lactating Women
Vitamin C [Also containing Ascorbic Acid Precursors as (1) Acid Metabolites including niacinamide ascorbate, calcium ascorbate, magnesium ascorbate, potassium ascorbate and sodium ascorbate; (2) Basic Amino Acids including lysine acetate; (3) Flavonoids including hesperidin; and (4) Glutathione.] | 25 mg | 42%
Thiamine Mononitrate (B1) | 2 mg | 118%
Riboflavin (B2) | 3 mg | 150%
Niacin (B3) | 1.8 mg | 9%
Pyridoxine HCl (B6) | 25 mg | 1000%
Folic Acid | 1 mg | 125%
Cyanocobalamin (B12) | 12.5 mcg | 156%
Biotin (B7) | 300 mcg | 100%
d-Calcium Pantothenate (B5) | 5 mg | 50%
Ferrous Fumarate (anhydrous) (Equivalent to about 17.5 mg of Elemental iron) | 53.5 mg [Minimum Iron Salt content.]
Polysaccharide Iron Complex (Equivalent to about 17.5 mg of Elemental iron) | 38 mg | [Total Iron: Ferrous Fumarate + Polysaccharide Iron Complex.] 194%
Magnesium (as magnesium sulfate) | 5 mg | 1%
Zinc (as zinc sulfate) | 10 mg | 67%
Copper (as copper sulfate) | 2 mg | 100%
Omega-3 Fatty Acids [At least 200 mg Omega-3 Fatty Acids derived from 310 mg fish oil.] | 200 mg | [Daily Value not established.]
Docosahexaenoic Acid (DHA) | 156 mg
Eicosapentaenoic Acid (EPA) | 39 mg

Other Ingredients: Lecithin, Beeswax, Soybean Oil, Caramel, Capsule (Gelatin, Glycerin, Water, and Caramel). Contains Soy and Fish Oil.

DOSAGE AND ADMINISTRATION

1 softgel daily, in between meals, or as prescribed by a licensed medical practitioner regardless of lactation status.

CAUTION

Ingestion of more than 3 grams per day of omega-3 fatty acids (ALA, EPA, and DHA) may have potential antithrombotic activities, or effects, and may increase bleeding times. Administration of omega-3 fatty acids, including DHA, should be avoided in patients with inherited or acquired bleeding diathesis, including those taking anticoagulants. Exercise caution to ensure that the prescribed dosage of DHA does not exceed 1 gram (1000 mg) per day.

WARNINGS

WARNING: Accidental overdose of iron-containing products is a leading cause of fatal poisoning in children under 6. Keep this product out of reach of children. In case of accidental overdose, call a doctor or poison control center immediately.

CAUTION

High levels of folic acid may, especially in older adults, hide signs of Vitamin B-12 deficiency (such as pernicious anemia), a condition that that can cause nerve damage.

HEALTH CLAIM

Store at controlled room temperature 20°-25°C (68°-77°F); excursions permitted to 15°-30°C (59°-86°F). Protect from light and moisture. Dispense in a tight, light-resistant container.

HEALTH CLAIM

Call your licensed medical practitioner about side effects. You may report side effects by calling Virtus at 1-888-848-3593 or FDA at 1-800-FDA-1088.

HOW SUPPLIED

Supplied as oblong, dark black color softgel imprinted with "V355" dispensed in 30 count bottles.

HEALTH CLAIM

Manufactured for:
Virtus Pharmaceuticals, LLC
Langhorne, PA 19047
1-888-848-3593
Rev. 07/2019

PRINCIPAL DISPLAY PANEL - 30 Softgel Bottle Label

VIRTUS®
PHARMACEUTICALS

76439-331-30

Virt-C DHA

PRENATAL/POSTNATAL

Prescription Folic Acid-Containing
Dietary Supplement
with Omega-3 Fatty Acids

RX

30 Softgels
Made in the USA